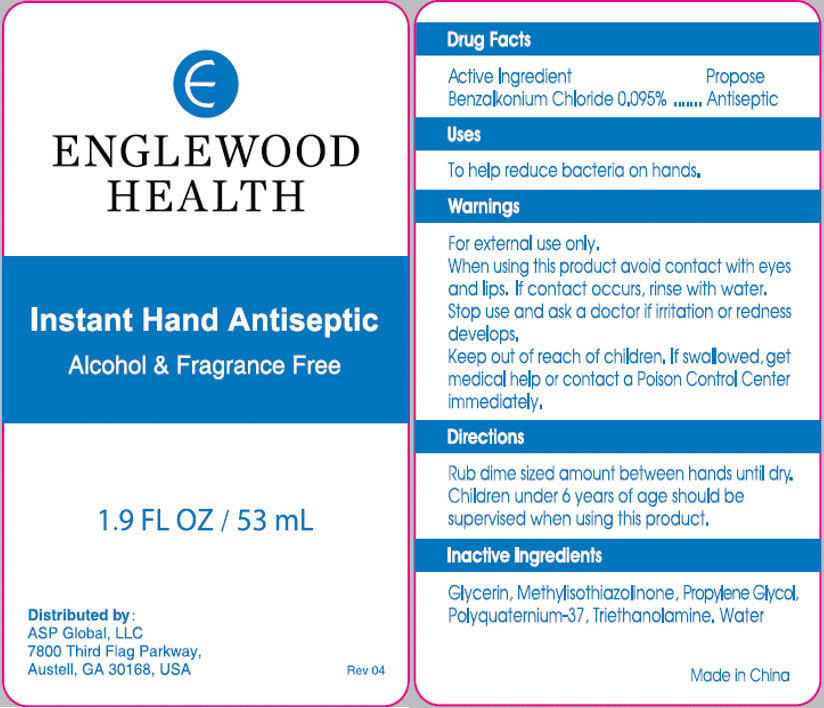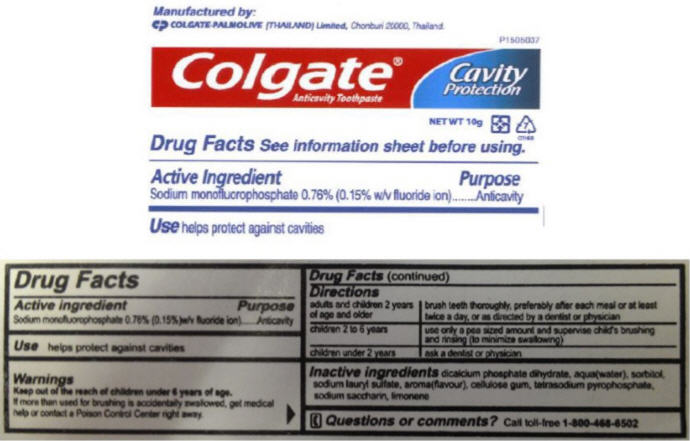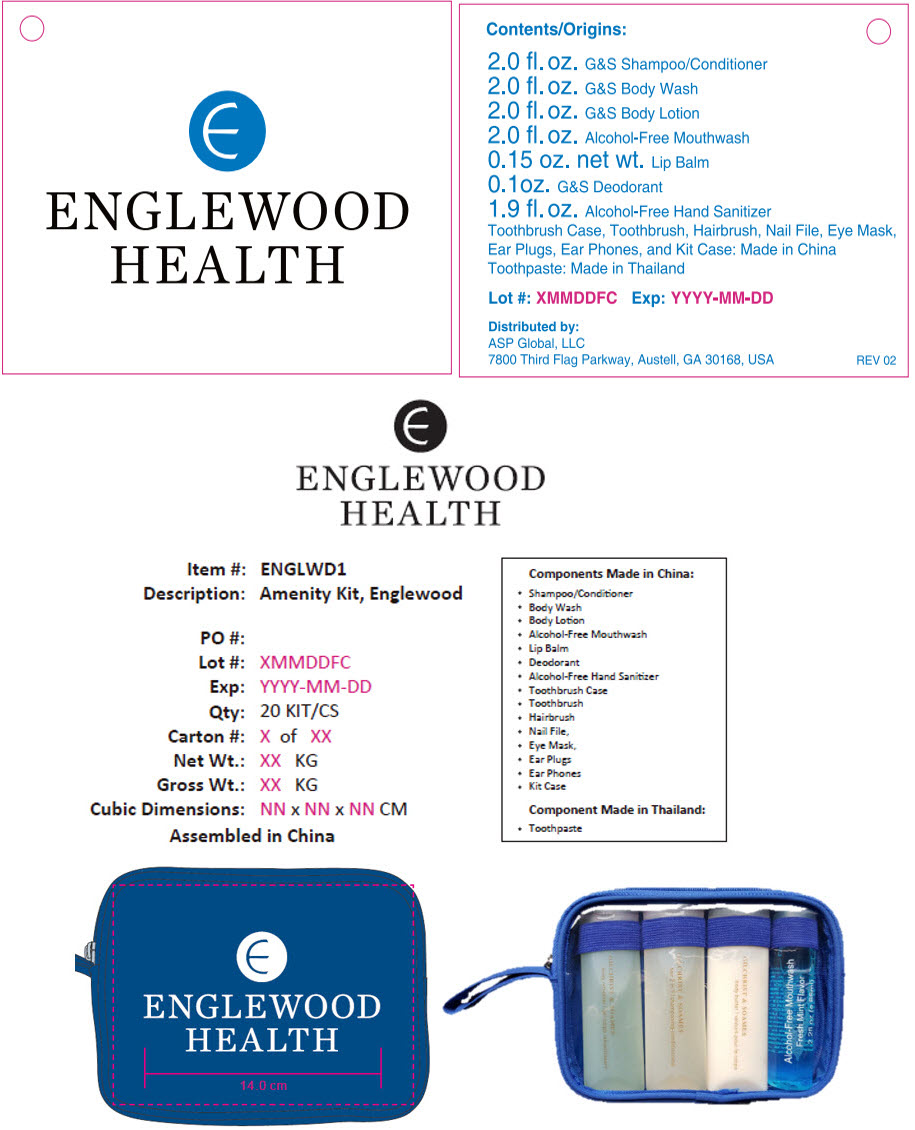 DRUG LABEL: Englewood Amenity
NDC: 59448-400 | Form: KIT | Route: TOPICAL
Manufacturer: ASP Global, LLc
Category: otc | Type: HUMAN OTC DRUG LABEL
Date: 20241217

ACTIVE INGREDIENTS: Benzalkonium Chloride 0.095 mg/100 mL; SODIUM MONOFLUOROPHOSPHATE 7.6 mg/1 g
INACTIVE INGREDIENTS: Water; POLYQUATERNIUM-37 (25000 MPA.S); Glycerin; Propylene Glycol; Methylisothiazolinone; Trolamine; DIBASIC CALCIUM PHOSPHATE DIHYDRATE; Water; Sorbitol; Sodium Lauryl Sulfate; SODIUM PYROPHOSPHATE; SACCHARIN SODIUM

Englewood Amenity Kit

Instant Hand Antiseptic

Drug Facts

Active Ingredient

Benzalkonium Chloride 0.095%

Purpose

Antiseptic

Uses

To help reduce bacteria on hands.

Warnings

For external use only.

When using this product avoid contact with eyes and lips. If contact occurs, rinse with water.

Stop use and ask a doctor if irritation or redness develops.

Keep out of reach of children. If swallowed, get medical help or contact a Poison Control Center immediately.

Directions

Rub dime sized amount between hands until dry.

Children under 6 years of age should be supervised when using this product.

Inactive Ingredients

Glycerin, Methylisothiazolinone, Propylene Glycol, Polyquaternium-37, Triethanolamine. Water

Distributed by:
ASP Global, LLC
7800 Third Flag Parkway,
Austell, GA 30168, USA

Colgate® Anticavity Toothpaste

Drug Facts

Active ingredient

Sodium monofluorophosphate 0.76% (0.15%) w/v fluoride ion)

Purpose

Anticavity

Use

helps protect against cavities

Warnings

KEEP OUT OF REACH OF CHILDREN

Keep out of the reach of children under 6 years of age.

If more than used for brushing is accidentally swallowed, get medical help or contact a Poison Control Center right away.

Directions

adults and children 2 years of age and older | brush teeth thoroughly, preferably after each meal or at least twice a day, or as directed by a dentist or physician
children 2 to 6 years | use only a pea sized amount and supervise child's brushing and rinsing (to minimize swallowing)
children under 2 years | ask a dentist or physician

Inactive ingredients

dicalcium phosphate dihydrate, water, sorbitol, sodium lauryl sulfate, flavor, cellulose gum, tetrasodium pyrophosphate, sodium saccharin

Questions or comments?

Call toll-free 1-800-468-6502

Manufactured by:

COLGATE-PALMOLIVE (THAILAND) Limited, Chonburi 20000, Thailand.

PRINCIPAL DISPLAY PANEL - 53 mL Bottle Label

ENGLEWOOD
HEALTH

Instant Hand Antiseptic

Alcohol & Fragrance Free

1.9 FL OZ / 53 mL

Distributed by:
ASP Global, LLC
7800 Third Flag Parkway,
Austell, GA 30168, USA

Rev 04

PRINCIPAL DISPLAY PANEL - 10 g Tube Label

PT505037

Colgate®
Anticavity Toothpaste

Cavity
Protection

NET WT 10g

7
OTHER

PRINCIPAL DISPLAY PANEL - Kit Label

ENGLEWOOD
HEALTH

Contents/Origins:

2.0 fl.oz. G&S Shampoo/Conditioner
2.0 fl.oz. G&S Body Wash
2.0 fl.oz. G&S Body Lotion
2.0 fl.oz. Alcohol-Free Mouthwash
0.15 oz. net wt. Lip Balm
0.1 oz. G&S Deodorant
1.9 fl.oz. Alcohol-Free Hand Sanitizer
Toothbrush Case, Toothbrush, Hairbrush, Nail File, Eye Mask,
Ear Plugs, Ear Phones, and Kit Case: Made in China
Toothpaste: Made in Thailand

Lot #: XMMDDFC Exp: YYYY-MM-DD

Distributed by:
ASP Global, LLC
7800 Third Flag Parkway, Austell, GA 30168, USA
REV 02

ENGLEWOOD
HEALTH

Item #: ENGLWD1
Description: Amenity Kit, Englewood

PO #:
Lot #: XMMDDFC
Exp: YYYY-MM-DD
Qty: 20 KIT/CS
Carton #: X of XX
Net Wt.: XX KG
Gross Wt.: XX KG
Cubic Dimensions: NN x NN x NN CM

Assembled in China

Components Made in China:

- Shampoo/Conditioner
- Body Wash
- Body Lotion
- Alcohol-Free Mouthwash
- Lip Balm
- Deodorant
- Alcohol-Free Hand Sanitizer
- Toothbrush Case
- Toothbrush
- Hairbrush
- Nail File,
- Eye Mask,
- Ear Plugs
- Ear Phones
- Kit Case

Component Made in Thailand:

- Toothpaste

ENGLEWOOD
HEALTH